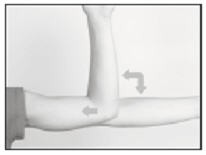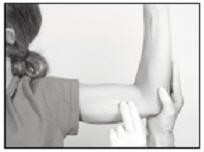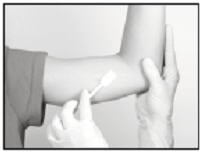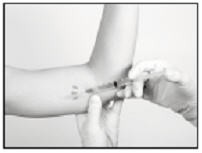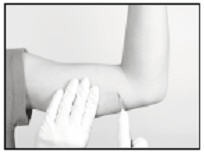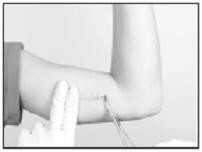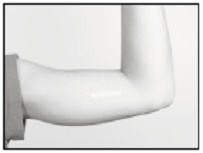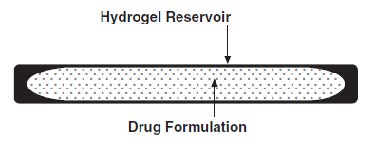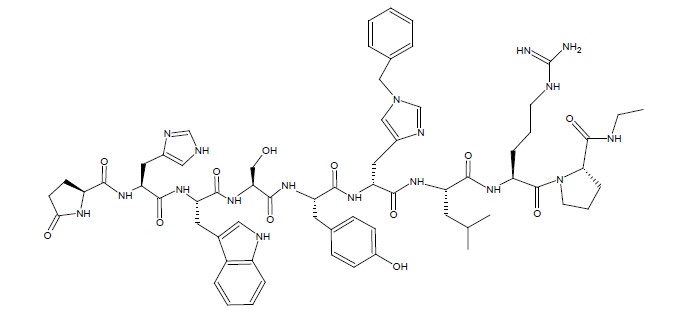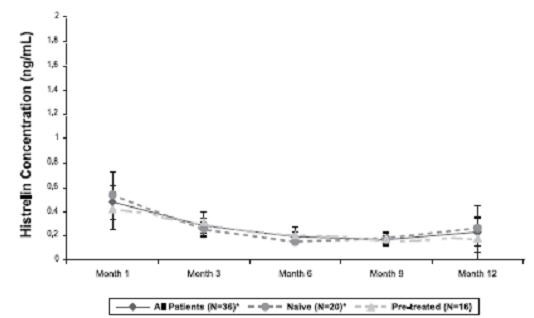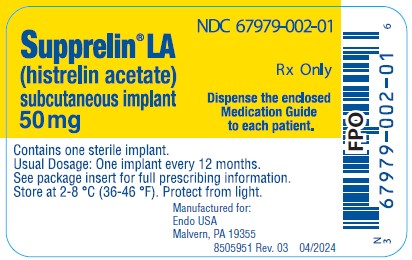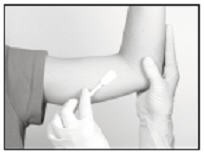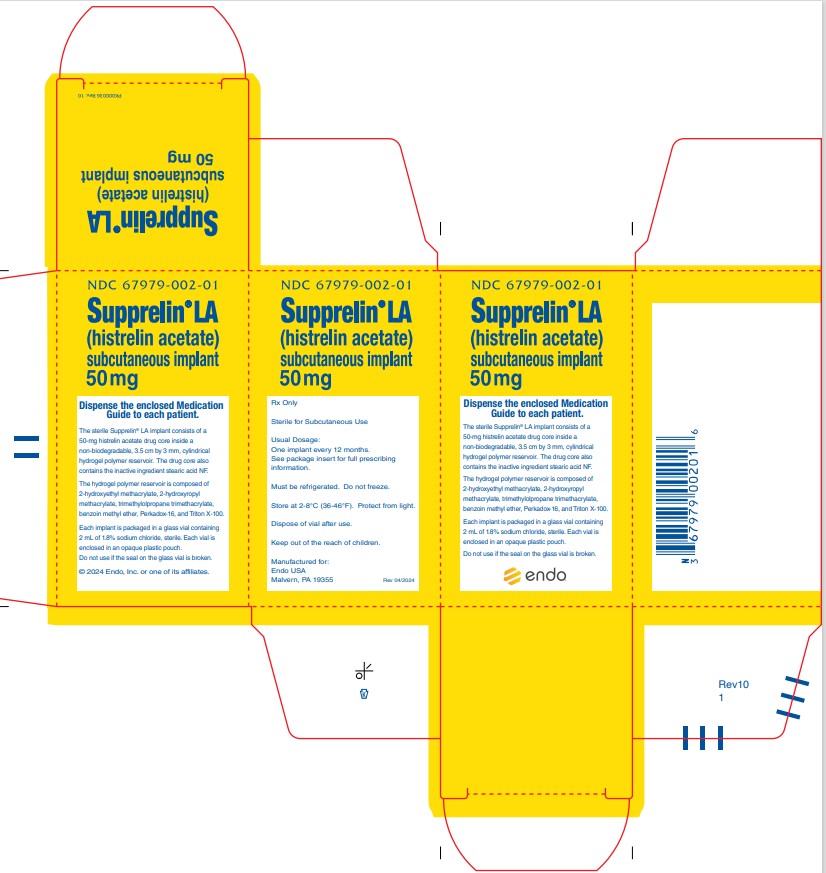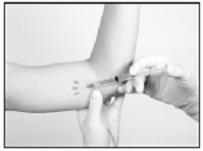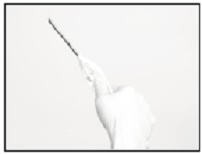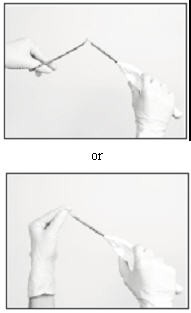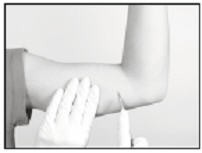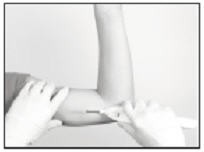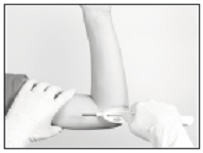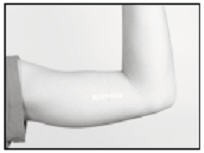 DRUG LABEL: SUPPRELIN
NDC: 67979-002 | Form: IMPLANT
Manufacturer: Endo USA, Inc.
Category: prescription | Type: HUMAN PRESCRIPTION DRUG LABEL
Date: 20250925

ACTIVE INGREDIENTS: HISTRELIN ACETATE 50 mg/1 1
INACTIVE INGREDIENTS: STEARIC ACID; 2-HYDROXYETHYL METHACRYLATE; METHYL BENZOIN; DI-(4-TERT-BUTYLCYCLOHEXYL)PEROXYDICARBONATE; OCTOXYNOL 9

HIGHLIGHTS OF PRESCRIBING INFORMATION

These highlights do not include all the information needed to use SUPPRELIN® LA safely and effectively. See full prescribing information for SUPPRELIN® LA.
SUPPRELIN LA (histrelin acetate) subcutaneous implant
Initial U.S. Approval: 1991

RECENT MAJOR CHANGES

Warnings and Precautions, Severe Cutaneous Adverse Reactions (5.5) 09/2025

1 INDICATIONS AND USAGE

SUPPRELIN LA is a gonadotropin releasing hormone (GnRH) agonist indicated for the treatment of children with central precocious puberty (CPP) (1).

2 DOSAGE AND ADMINISTRATION

The recommended dose of SUPPRELIN LA is one implant every 12 months. The implant is inserted subcutaneously in the inner aspect of the upper arm and provides continuous release of histrelin for 12 months of hormonal therapy (2).

3 DOSAGE FORMS AND STRENGTHS

SUPPRELIN LA is available as a 50 mg histrelin acetate subcutaneous implant which delivers approximately 65 mcg histrelin acetate per day over 12 months (3).

4 CONTRAINDICATIONS

- History of hypersensitivity to gonadotropin releasing hormone (GnRH) or GnRH analogs (4).
- Pregnancy (4).

5 WARNINGS AND PRECAUTIONS

- Initial Agnostic Action: Initial transient increases of estradiol and/or testosterone may cause a temporary worsening of symptoms (5.1).
- Implant Breakage: Have been observed during implant removal. Monitor luteinizing hormone, follicle stimulating hormone or testosterone for suppression of CPP (5.2, 5.6)
- Psychiatric Events: Have been reported in patients taking GnRH agonists. Events include emotional lability, such as crying, irritability, impatience, anger, and aggression. Monitor for development or worsening of psychiatric symptoms. (5.3)
- Convulsions: Have been observed in patients receiving GnRH agonists with or without a history of seizures, epilepsy, cerebrovascular disorders, central nervous system anomalies or tumors, and in patients on concomitant medications that have been associated with convulsions. (5.4)
- Severe Cutaneous Adverse Reactions: Have been reported in patients receiving GnRH agonists. Interrupt SUPPRELIN LA if signs or symptoms of severe cutaneous adverse reactions develop. Permanently discontinue SUPPRELIN LA if a severe cutaneous adverse reaction is confirmed. (5.5)
- Pseudotumor Cerebri (Idiopathic Intracranial Hypertension): Have been reported in pediatric patients receiving GnRH agonists. Monitor patients for headache, papilledema, and blurred vision. (5.6)

6 ADVERSE REACTIONS

- The most common adverse reaction is implant site reaction (51.1%), including complications related to the insertion or removal of the implant (6).
- Adverse events related to suppression of endogenous sex steroid secretion may occur (6.1).

To report SUSPECTED ADVERSE REACTIONS, contact Endo at 1-800-462-3636 or FDA at 1-800-FDA-1088 or www.fda.gov/medwatch.

8 USE IN SPECIFIC POPULATIONS

Use of SUPPRELIN LA in children less than 2 years of age is not recommended (8.4).

FULL PRESCRIBING INFORMATION

1 INDICATIONS AND USAGE

SUPPRELIN LA (histrelin acetate) subcutaneous implant is indicated for the treatment of children with central precocious puberty (CPP).

Children with CPP (neurogenic or idiopathic) have an early onset of secondary sexual characteristics (earlier than 8 years of age in females and 9 years of age in males). They also show a significantly advanced bone age that can result in diminished adult height attainment.

Prior to initiation of treatment a clinical diagnosis of CPP should be confirmed by measurement of blood concentrations of total sex steroids, luteinizing hormone (LH) and follicle stimulating hormone (FSH) following stimulation with a GnRH analog, and assessment of bone age versus chronological age. Baseline evaluations should include height and weight measurements, diagnostic imaging of the brain (to rule out intracranial tumor), pelvic/testicular/adrenal ultrasound (to rule out steroid secreting tumors), human chorionic gonadotropin levels (to rule out a chorionic gonadotropin secreting tumor), and adrenal steroids to exclude congenital adrenal hyperplasia.

2 DOSAGE AND ADMINISTRATION

2.1 Recommended Dose

The recommended dose of SUPPRELIN LA is one implant every 12 months. Each implant contains 50 mg histrelin acetate. The implant is inserted subcutaneously in the inner aspect of the upper arm and provides continuous release of histrelin acetate (65 mcg/day) for 12 months of hormonal therapy. SUPPRELIN LA should be removed after 12 months of therapy (the implant has been designed to allow for a few additional weeks of histrelin acetate release, in order to allow flexibility of medical appointments). At the time an implant is removed, another implant may be inserted to continue therapy. Discontinuation of SUPPRELIN LA should be considered at the discretion of the physician and at the appropriate time point for the onset of puberty (approximately 11 years for females and 12 years for males).

2.2 Recommended Procedure for Implant Insertion and Removal

This procedure section is intended to provide guidance for the insertion and removal of SUPPRELIN LA. The actual procedure used, however, is at the discretion of the qualified healthcare provider performing the procedure.

Insertion of a new implant can proceed using the following Suggested Insertion Procedure. If a previous SUPPRELIN LA implant must first be removed, please see the Suggested Removal Procedure instructions below.

Suggested Insertion Procedure
The supplies necessary to insert the implant, including the Insertion Tool and local anesthetic, are provided in a separate Implantation Kit that is shipped along with the implant. Please note that the implant should be kept refrigerated (2-8°C) in its sealed vial, pouch, and carton, until needed for the procedure. Once removed from refrigeration, the vial containing the implant (still in its unopened pouch and carton) may remain at room temperature for up to 7 days, if necessary, before being used. If not used in that time, the packaged implant may again be properly refrigerated until the expiration date on the carton.

NOTE: The Implantation Kit is to be stored at room temperature and should not be refrigerated.

Insertion of the SUPPRELIN LA implant is a surgical procedure. Sterile gloves and aseptic technique must be used to minimize any chance of infection.

Setting up the Sterile Field
Using proper aseptic technique, the sterilized components of the Implantation Kit needed for the insertion procedure, including the Insertion Tool, are to be carefully dispensed from their packaging onto the Sterile Field drape (non-fenestrated) provided. NOTE THAT THE KIT BOX AND ALL PACKAGING ARE NOT STERILE and should be kept off of the Sterile Field drape. DO NOT PLACE THE VIAL OF LOCAL ANESTHETIC OR THE VIAL CONTAINING THE IMPLANT ONTO THE DRAPE as the exterior surface of these vials is not sterile.

The implant vial should not be opened until just before the time of insertion. Open the vial by removing the metal band and carefully pour the sterile contents (implant and sterile saline) onto the Sterile Field drape. The implant can then be handled with sterile gloves or with the sterile mosquito clamp provided. AVOID bending or pinching the implant.

Preparing the Patient and the Insertion Site
The patient should be on his/her back, ideally with the arm least used (e.g., left arm for a right-handed person) positioned, either bent or extended, so that the physician has ready access to the inner aspect of the upper arm. Propping the arm with pillows may help the patient more easily hold the position. The suggested optimum site for subcutaneous insertion is approximately half-way between the shoulder and the elbow, in line with the crease between the biceps and triceps muscles.

Antiseptic
Swab the insertion area with topical antiseptic, then overlay with the fenestrated Sterile Field drape provided, so that the opening is over the insertion site (for clarity of illustration, the following images do not show the drape).

Anesthetic
The method of anesthesia utilized (i.e., local, conscious sedation, general) is at the discretion of the healthcare provider.

If local anesthesia is selected: a vial of sterile local anesthetic (note that the exterior of the vial is not sterile) has been provided along with a sterile hypodermic needle for injection. After determining the absence of known allergies to the anesthetic agent, inject anesthetic into the subcutaneous tissue, starting at the planned incision site, then infiltrating along the intended subcutaneous insertion path, up to the length of the implant (a little more than one inch). Local anesthesia may also be supplemented by the use of distraction techniques.

The following sections describe the suggested procedure for insertion of the implant using the Insertion Tool provided. The method of insertion used, however, is at the discretion of the healthcare provider performing the procedure.

Loading the Insertion Tool
The sterile Insertion Tool is comprised of a fixed handle attached to a retractable, bevel-tipped cannula, into the chamber of which the implant is to be placed for subcutaneous insertion. The cannula can be extended and retracted. The fully extended cannula contains a fixed piston upon which the implant, once inserted, rests. During the final step of the insertion procedure, the cannula will be retracted into the handle using the slide mechanism (green button), thereby exposing and leaving the implant to remain in the subcutaneous tissue.

When first grasping the sterile Insertion Tool, confirm that the cannula is fully extended. Verify this by inspecting the position of the green retraction button. The button should be locked in position all the way forward, towards the cannula, farthest from the handle.

The implant can be picked up using sterile gloves or with the sterile mosquito clamp provided. Avoid bending or pinching the implant. Note that the implant may come out of its vial slightly curved and/or partially flattened after refrigerated storage. To help make the implant more symmetrical prior to loading into the Tool, you can roll the implant a few times (while wearing a sterile glove) between the fingers and thumb.

Insert the implant into the cannula of the Insertion Tool manually or using the mosquito clamp. When inserting the implant into the cannula, DO NOT FORCE the implant. If resistance is felt, the implant should be removed and manually manipulated or rolled as needed, and re-inserted into the cannula.

When fully inserted, the implant rests inside the cannula so that just the tip of the implant is visible at the beveled end of the cannula.

Making the Incision
Using the sterile scalpel provided, make an incision transverse to the long axis of the arm, and of a size adequate to allow the bore of the cannula to be inserted into the subcutaneous tissue. Be sure that the incision is positioned so that there is sufficient length of upper arm available to fit the implant easily within the intended insertion space.

Inserting the Implant
It is suggested that insertion may be easier if a “pocket” for the implant is first created by blunt dissection through the incision, subcutaneously along the path of the anesthetic, using the cannula of the loaded Insertion Tool, or using a sterile hemostatic clamp or equivalent surgical tool.

Be sure to VISIBLY RAISE THE SKIN (known as tenting) at all times during the pocket-making and insertion procedures to ensure correct subcutaneous placement (“just under the skin”) of the implant. Note that the cannula of the Insertion Tool, or whatever tool is being used to create the pocket, SHOULD NOT ENTER MUSCLE TISSUE. Deep insertion of the implant will not affect the performance of SUPPRELIN LA, but may cause difficulty in the later removal of the implant.

If using the cannula of the loaded Insertion Tool to create the pocket, carefully insert the tip of the cannula into the incision and advance through the subcutaneous tissue, while visibly raising the skin along the length of the cannula up to, but no farther than, the inscribed black line on the cannula. DO NOT DEPRESS THE GREEN RETRACTION BUTTON ON THE TOOL WHILE INSERTING OR ADVANCING THE TOOL INTO THE INCISION.

Pull the Tool back, almost to the beveled tip of the cannula, and advance the Tool forward again, so that the cannula re-enters the pocket completely, but no farther than the inscribed black line. Be sure to keep the insertion path just immediately subcutaneous.

If another tool was used to create the pocket, now insert the loaded cannula of the Insertion Tool containing the implant through the incision, up to the inscribed black line.

Hold the Insertion Tool in place with the base against the patient’s arm (if possible) as you carefully move your thumb to the green retraction button. Depress the button to release the locking mechanism, then slide the button back toward the handle until it stops, all the while holding the body of the Insertion Tool in place.

Retracting the button causes the cannula to withdraw from the incision, leaving the implant in the subcutaneous tissue. DO NOT FURTHER ADVANCE THE CANNULA ONCE THE RETRACTION PROCESS HAS STARTED. Likewise, do not withdraw the Insertion Tool until the button is fully retracted or the implant may be pulled partially out of the incision. Once the retraction is complete, the Tool can be fully withdrawn.

NOTE: It may be helpful during the process of retraction and withdrawal of the cannula to apply pressure to the skin over the implant, to help ensure that the implant remains in the subcutaneous pocket.

If there is a need to re-start the process at any time during the insertion procedure, withdraw the Insertion Tool, carefully extract the implant from the cannula and reset the retraction button on the Tool to its forward-most position. Examine the implant before reloading the implant into the Insertion Tool, and start again.

Placement of the implant should be confirmed by palpation. Note that the tip of a properly-placed implant may not be visible through the incision.

After implantation, briefly cover the site with a sterile gauze pad and apply pressure to ensure hemostasis.

Closing the Incision
To close the incision, you can use the absorbable sutures and/or the sterile adhesive surgical strips provided. To improve adhesion of the strips, you can apply benzoin tincture antiseptic (provided) to the skin, and let it dry, before applying the adhesive strips.

Once closed, cover the incision site with sterile gauze pads and secure the dressing with the bandage provided.

Please provide the patient’s parent or guardian with a Patient Information Leaflet, which includes information about the implant and instructions on proper care of the insertion site.

Suggested Removal Procedure
SUPPRELIN LA should be removed after 12 months of therapy. Most of the supplies necessary to remove the implant, including the local anesthetic and the sterile mosquito clamp, are provided in the Implantation Kit that is shipped along with a new SUPPRELIN LA implant. Note that the Implantation Kit is to be stored at room temperature and must not be refrigerated. See the Suggested Insertion Procedure above for further instructions.

Removal of the SUPPRELIN LA implant is a surgical procedure. Sterile gloves and aseptic technique must be used to minimize any chance of infection.

Setting up the Sterile Field
Using proper aseptic technique, the sterilized components of the Implantation Kit needed for the implant removal procedure are to be carefully dispensed from their packaging out onto the Sterile Field drape (non-fenestrated) provided. NOTE THAT THE KIT BOX AND ALL PACKAGING ARE NOT STERILE and should be kept off of the Sterile Field drape. DO NOT PLACE THE VIAL OF LOCAL ANESTHETIC ONTO THE DRAPE as the exterior surface of the vial is not sterile.

Preparing the Patient and the Site
The patient should be on his/her back, with the arm containing the implant positioned, either bent or extended, so that the physician has ready access to the inner aspect of the upper arm. Propping the arm with pillows may help the patient more easily hold the position.

The implant to be removed should first be located by palpating the inner aspect of the upper arm, near the incision from the prior year.

Generally, the previous implant is readily palpated. In the event the implant is difficult to locate, ultrasound may be used. If ultrasound fails to locate the implant, other imaging techniques such as CT or MRI may be used to locate it (plain films are not recommended as the implant is not radiopaque).

Antiseptic
Swab the area above and around the previous implant with topical antiseptic. Overlay the area with the fenestrated Sterile Field drape provided, so that the hole is over the previous insertion site (for clarity of illustration, the following images do not show the drape).

Anesthetic
The method of anesthesia utilized (i.e., local, conscious sedation, general) is at the discretion of the healthcare provider.

If local anesthesia is selected: a vial of sterile local anesthetic (note that the exterior of the vial is not sterile) has been provided along with a sterile hypodermic needle for injection. After determining the absence of known allergies to the anesthetic agent, inject anesthetic into the subcutaneous tissue at and around the site of the intended incision (the site of the previous implant). Local anesthesia may also be supplemented by the use of distraction techniques.

Making the Incision and Removing the Implant
Using the sterile scalpel provided, make an incision of a size adequate to allow the implant to be easily removed and, if a new implant will be inserted, large enough for the bore of the cannula of the Insertion Tool provided.

Generally, the tip of the implant will be visible through the incision, possibly covered by a pseudocapsule of tissue. In order to facilitate the removal of the implant, it may be necessary to palpate the head of the implant through the incision using your smallest finger, especially if the head of the implant is not readily visible. In addition, you may need to push down on the distal end of the implant and “massage it forward” towards the incision.

Carefully nick the pseudocapsule to reveal the polymer tip of the implant. It may be beneficial to insert the sterile mosquito clamp provided into the hole created in the pseudocapsule and expand by opening the clamp. Widening the opening of the pseudocapsule may ease the extraction of the implant.

Gently but securely grasp the implant with the sterile mosquito clamp and extract the implant.

Dispose of the implant in a proper manner, treating it like any other bio-waste.

Briefly cover the site with a sterile gauze pad and apply pressure to ensure hemostasis.

If inserting a new implant, see the Suggested Insertion Procedure instructions provided above. Note that you can insert the new implant into the same “pocket” as the removed implant, or make a new incision at a different site in the same arm or in the contralateral arm.

If a new implant is not to be inserted, proceed to close the incision.

Closing the Incision
To close the incision, you can use the absorbable sutures and/or the sterile adhesive surgical strips provided. To improve adhesion of the strips, you can apply benzoin tincture antiseptic (provided) to the skin, and let it dry, before applying the adhesive strips.

Once closed, cover the incision site with sterile gauze pads and secure the dressing with the bandage provided.

3 DOSAGE FORMS AND STRENGTHS

SUPPRELIN LA is a sterile, nonbiodegradable, diffusion-controlled, hydrogel polymer reservoir drug delivery system designed to deliver histrelin acetate continuously for 12 months after subcutaneous implantation. The sterile implant contains 50 mg histrelin acetate and delivers approximately 65 mcg histrelin acetate per day over 12 months.

4 CONTRAINDICATIONS

SUPPRELIN LA is contraindicated in:

- Patients who are hypersensitive to gonadotropin releasing hormone (GnRH) or GnRH agonist analogs
- Pregnancy [see Use in Specific Populations (8.1)].

5 WARNINGS AND PRECAUTIONS

5.1 Initial Agonistic Action

SUPPRELIN LA, like other GnRH agonists, initially causes a transient increase in serum concentrations of estradiol in females and testosterone in both sexes during the first week of treatment. Patients may experience worsening of symptoms or onset of new symptoms during this period. However, within 4 weeks of histrelin therapy, suppression of gonadal steroids occurs and manifestations of puberty decrease.

5.2 Implant Breakage

Implant insertion is a surgical procedure and it is important that the insertion instructions are followed to avoid potential complications. The insertion and removal of the implant should be done aseptically. Proper surgical technique is critical in minimizing adverse events related to the insertion and the removal of the histrelin implant. On occasion, localizing and/or removal of implant products have been difficult and imaging techniques were used, including ultrasound, CT, or MRI (note: the histrelin implant is not radiopaque). In some cases the implant broke during removal and multiple pieces were recovered. Confirm that the entire implant has been removed. If the implant was not retrieved completely, the remaining pieces should be removed following the instructions in the Suggested Removal Procedure section [see Dosage and Administration (2.2)]. Rare events of spontaneous extrusion of the implant have been observed in clinical trials. During SUPPRELIN LA treatment, patients should be evaluated for evidence of clinical and biochemical suppression of CPP manifestations (see Section 5.6, Monitoring and Laboratory tests). Detailed instructions on the insertion and removal procedures of the implant are provided above [see Dosage and Administration (2.2)].

5.3 Psychiatric Events

Psychiatric events have been reported in patients taking GnRH agonists, including SUPPRELIN LA. Postmarketing reports with this class of drugs include symptoms of emotional lability, such as crying, irritability, impatience, anger, and aggression. Monitor for development or worsening of psychiatric symptoms during treatment with SUPPRELIN LA [see Adverse Reactions (6)].

5.4 Convulsions

Postmarketing reports of convulsions have been observed in patients receiving GnRH agonists, including SUPPRELIN LA. Reports with GnRH agonists have included patients with a history of seizures, epilepsy, cerebrovascular disorders, central nervous system anomalies or tumors, and patients on concomitant medications that have been associated with convulsions such as bupropion and SSRIs. Convulsions have also been reported in patients in the absence of any of the conditions mentioned above.

5.5 Severe Cutaneous Adverse Reactions

Severe cutaneous adverse reactions have been reported in patients receiving GnRH agonists [see Adverse Reactions (6.3)]. These reactions include Stevens-Johnson syndrome/toxic epidermal necrolysis (SJS/TEN), drug reaction with eosinophilia and systemic symptoms (DRESS), and acute generalized exanthematous pustulosis (AGEP), including cases with visceral involvement and/or requiring skin grafts.

Monitor patients for signs and symptoms of severe cutaneous adverse reactions such as fever, flu-like symptoms, mucosal lesions, progressive skin rash or lymphadenopathy. Advise patients and caregivers of the signs and symptoms of severe cutaneous adverse reactions.

If a severe cutaneous adverse reaction is suspected, interrupt SUPPRELIN LA. Consult a healthcare provider with expertise in the diagnosis and management of severe cutaneous adverse reactions. If a diagnosis of severe cutaneous adverse reaction is confirmed permanently discontinue SUPPRELIN LA.

5.6 Pseudotumor Cerebri (Idiopathic Intracranial Hypertension)

Pseudotumor cerebri (idiopathic intracranial hypertension) have been reported in pediatric patients receiving GnRH agonists. Monitor patients for signs and symptoms of pseudotumor cerebri, including headache, papilledema, blurred vision, diplopia, loss of vision, pain behind the eye or pain with eye movement, tinnitus, dizziness, and nausea.

5.7 Monitoring and Laboratory Tests

LH, FSH and estradiol or testosterone should be monitored at 1 month post implantation then every 6 months thereafter. Additionally, height (for calculation of height velocity) and bone age should be assessed every 6-12 months.

6 ADVERSE REACTIONS

The following serious adverse reactions are described here and elsewhere in the label:

- Initial Agonist Action [see Warnings and Precautions (5.1)]
- Implant Breakage [see Warnings and Precautions (5.2)]
- Psychiatric Events [see Warnings and Precautions (5.3)]
- Convulsions [see Warnings and Precautions (5.4)]
- Severe Cutaneous Adverse Reactions [see Warnings and Precautions (5.5)]
- Pseudotumor Cerebri (Idiopathic Intracranial Hypertension) [see Warnings and Precautions (5.6)]

6.1 Overall Adverse Reaction Profile

The most common adverse reactions with SUPPRELIN LA involved the implant site. Local reactions after implant insertion include bruising, pain, soreness, erythema and swelling.

During the early phase of therapy, gonadotropins and sex steroids rise above baseline because of the natural stimulatory effect of the drug. Therefore, an increase in clinical signs and symptoms may be observed [see Warnings and Precautions (5.1)].

6.2 Adverse Reactions in Clinical Trials

Because clinical trials are conducted under widely varying conditions, adverse reaction rates observed in the clinical trials of a drug cannot be directly compared to rates in the clinical trials of another drug and may not reflect the rates observed in practice.

The safety of SUPPRELIN LA in children with CPP was evaluated in two single-arm clinical trials conducted in a total of 47 patients (44 females and 3 males) over a period of time ranging from 9 to 18 months. The most commonly reported adverse reaction was implant site reaction, which was reported by 24 of 47 (51.1%) patients. Implant site reaction includes discomfort, bruising, soreness, pain, tingling, itching, implant area protrusion and swelling. Two subjects experienced a serious adverse reaction: 1 subject who coincidentally had Stargardt’s Disease experienced amblyopia and 1 subject had a benign pituitary tumor (pituitary adenoma). One subject discontinued the study due to an adverse reaction of infection at the implant site. There were no clinically meaningful findings in standard clinical hematology and chemistry tests and/or in vital signs. The incidence of implantation adverse events reported by more than 2 patients are summarized in Table 1.

Table 1: Incidence of implantation adverse reactions reported by ≥ 2 patients treated with SUPPRELIN LA in both clinical trials
Adverse Reactions | N=47 N (%)
Implant site reaction | 24 (51.1)
Keloid scar | 3 (6.4)
Scar | 3 (6.4)
Suture related complication | 3 (6.4)
Application site pain | 2 (4.3)
Post procedural pain | 2 (4.3)

The following adverse reactions were reported as possibly related or related in 1 patient each: wound infection, breast tenderness, dysmenorrhea, epistaxis, erythema, feeling cold, gynecomastia, headache, menorrhagia, migraine, mood swings, pituitary tumor benign, pruritus, weight increased, disease progression and influenza-like illness. The adverse reaction metrorrhagia was reported as possibly related or related in 2 patients.

6.3 Post-marketing Experience

The following adverse reactions have been identified during post approval use of SUPPRELIN LA or GnRH agonists. Because these reactions are reported voluntarily from a population of uncertain size, it is not always possible to reliably estimate their frequency or establish a causal relationship to drug exposure.

General Disorders and Administration Site Conditions: implant breakage

Psychiatric Disorders: Emotional lability, such as crying, irritability, impatience, anger, and aggression. Depression, including rare reports of suicidal ideation and attempt. Many, but not all, of these patients had a history of psychiatric illness or other comorbidities with an increased risk of depression.

Nervous System Disorders: seizures. Pseudotumor cerebri (idiopathic intracranial hypertension) have been observed with GnRH agonists.

Skin Reactions: erythema multiforme, bullous dermatitis, dermatitis exfoliative, drug reaction with eosinophilia and systemic symptoms, Stevens-Johnson syndrome and toxic epidermal necrolysis, and acute generalized exanthematous pustulosis.

7 DRUG INTERACTIONS

Overview: No formal drug-drug, drug-food, or drug-herb interaction studies were performed with SUPPRELIN LA.

Drug-Laboratory Interactions: Therapy with SUPPRELIN LA results in suppression of the pituitary-gonadal system. Results of diagnostic tests of pituitary gonadotropic and gonadal functions conducted during and after SUPPRELIN LA therapy may be affected. SUPPRELIN LA decreased mean serum insulin like growth factor 1 (IGF 1) levels by approximately 11% in one study (Study 1). SUPPRELIN LA increased the serum concentration of dehydroepiandrosterone (DHEA) in 8 of 36 patients in another study (Study 2).

8 USE IN SPECIFIC POPULATIONS

8.1 Pregnancy

Risk Summary

SUPPRELIN LA is contraindicated during pregnancy [see Contraindications (4)] since expected hormonal changes that occur with SUPPRELIN LA treatment increase the risk for pregnancy loss. The limited data with histrelin use in pregnant women are insufficient to determine a drug-associated risk for major birth defects or adverse developmental outcomes. Consistent with mechanism of action for SUPPRELIN LA [see Clinical Pharmacology (12.1)], animal reproduction studies showed an increase in fetal loss at clinically relevant exposures.

The estimated background risk of major birth defects and miscarriage for the indicated population is unknown. In the US general population, the estimated background risk of major birth defects and miscarriage in clinically recognized pregnancies is 2-4% and 15-20%, respectively.

Data

Animal Data

Histrelin acetate administered to pregnant rats during the period of organogenesis increased fetal mortality and post-implantation loss at doses of 1, 3, 5 or 15 mcg/kg/day, approximating clinical exposure based on body surface area. These dosages also reduced maternal body weight gain, stimulated ovarian follicular development, increased placental weight and caused abnormal morphology and an increase in fetal size. Histrelin acetate administered to pregnant rabbits during the period of organogenesis increased fetal mortality and abortion/early termination at the two highest doses and caused total litter loss at all doses of 20, 50 or 80 mcg/kg/day (approximately 3- to 12-times clinical exposures based on body surface area).

8.2 Lactation

Risk Summary

There are no data on the presence of SUPPRELIN LA in human or animal milk, the effects on the breastfed infant, or the effects on milk production. Absorption and systemic activity are not expected from potential exposure to the peptide, histrelin, in the breast milk. The developmental and health benefits of breastfeeding should be considered along with the mother’s clinical need for SUPPRELIN LA and any potential adverse effects on the breastfed child from SUPPRELIN LA or from the underlying maternal condition.

8.4 Pediatric Use

Safety and effectiveness in pediatric patients below the age of 2 years have not been established. The use of SUPPRELIN LA in children under 2 years is not recommended.

10 OVERDOSAGE

There have been no reports of overdose in SUPPRELIN LA clinical trials. High doses of histrelin acetate injection in animal studies were generally associated only with effects attributed to the expected pharmacology. The method of drug delivery makes accidental or intentional overdosage unlikely.

11 DESCRIPTION

SUPPRELIN LA is a sterile, non-biodegradable, diffusion-controlled, hydrogel polymer reservoir containing histrelin acetate, a synthetic nonapeptide analog of the naturally occurring gonadotropin releasing hormone (GnRH) possessing a greater potency than the natural sequence hormone. SUPPRELIN LA is designed to deliver approximately 65 mcg histrelin acetate per day over 12 months.

The SUPPRELIN LA implant looks like a small thin flexible tube and consists of a 50-mg histrelin acetate drug core inside a 3.5 cm by 3 mm, cylindrical, hydrogel polymer reservoir (Figure 1). The implant may appear partially to completely full with variation in color from off-white to light brown. The color may be uneven within the core.

Figure 1: SUPPRELIN LA Implant Diagram (not to scale)

The chemical name of histrelin acetate is: L-Pyroglutamyl-L-histidyl-L-tryptophyl-L-seryl-L-tyrosyl-N-benzyl-D-histidyl-L-leucyl-L-arginyl-L-proline N-ethylamide, acetate salt.

The molecular formula for histrelin acetate is C66H86N18O12 x 2 CH3COOH and its molecular weight is 1443.70 (or 1323.52 as free base). Histrelin is also chemically described as 5-oxo-L-prolyl-L-histidyl-L-tryptophyl-L-seryl-L-tyrosyl-Nt-benzyl-D-histidyl-L-leucyl-L-arginyl-N-ethyl-L-prolinamide diacetate. The chemical structure of the free base (histrelin) is represented below in Figure 2.

Figure 2: Structure of Histrelin

The drug core also contains the inactive ingredient stearic acid NF. The hydrogel polymer reservoir is a hydrophilic cartridge composed of 2-hydroxyethyl methacrylate, 2-hydroxypropyl methacrylate, trimethylolpropane trimethacrylate, benzoin methyl ether, Perkadox-16, and Triton X-100. Each implant is packaged hydrated in a glass vial containing 2 mL of sterile 1.8% sodium chloride solution, so that it is primed for immediate release of the drug upon insertion.

A single use, sterile, Insertion Tool is provided along with the implant that can be used for the placement of the SUPPRELIN LA implant into the subcutaneous tissue of the inner aspect of the upper arm. The Insertion Tool is enclosed in a sterile bag and is provided separately from the implant in the Implantation Kit [see Recommended Procedure for Implant Insertion and Removal (2.2)].

12 CLINICAL PHARMACOLOGY

12.1 Mechanism of Action

SUPPRELIN LA is a GnRH agonist and an inhibitor of gonadotropin secretion when given continuously. It delivers approximately 65 mcg histrelin acetate per day. Both animal and human studies indicate that following an initial stimulatory phase, chronic, subcutaneous administration of histrelin acetate desensitizes responsiveness of the pituitary gonadotropin which, in turn causes a reduction in ovarian and testicular steroidogenesis.

In humans, administration of histrelin acetate results in an initial increase in circulating levels of LH and FSH, leading to a transient increase in concentration of gonadal steroids (testosterone and dihydrotestosterone in males, and estrone and estradiol in premenopausal females).

However, continuous administration of histrelin acetate causes a reversible down-regulation of the GnRH receptors in the pituitary gland and desensitization of the pituitary gonadotropes. These inhibitory effects result in decreased levels of LH and FSH.

12.2 Pharmacodynamics

Long-term treatment with histrelin acetate suppresses the LH response to GnRH causing LH levels to decrease to prepubertal levels within 1 month of treatment. As a result, serum concentrations of sex steroids (estrogen or testosterone) also decrease. Consequently, secondary sexual development ceases to progress in most patients. Additionally, linear growth velocity is slowed which improves the chance of attaining predicted adult height.

12.3 Pharmacokinetics

Pharmacokinetics of histrelin after implantation of SUPPRELIN LA was evaluated in a total of 47 children with CPP (11 subjects in Study 1 and 36 subjects in Study 2). Patients were examined at 4 weeks after implant insertion and a few times throughout the treatment period. Median serum histrelin concentrations remained above the limit of quantification for the treatment period. Histrelin acetate levels were sustained throughout the study period for most subjects (Figure 3). The median of maximum serum histrelin concentrations over the study period was 0.43 ng/mL, which is expected to maintain gonadotropins at prepubertal levels. There was no apparent pharmacokinetic difference between naïve subjects to a LHRH agonist treatment and subjects who had previous treatment with a LHRH agonist (Figure 3).

Figure 3: Mean and Standard Deviation of Serum Histrelin Concentrations (ng/mL) Results at Each Visit

13 NONCLINICAL TOXICOLOGY

13.1 Carcinogenesis, Mutagenesis, Impairment of Fertility

Carcinogenicity studies were conducted in rats for 2 years at doses of 5, 25 or 150 mcg/kg/day (up to 11 times human exposures using body surface area comparisons, based on a 65 mcg/day dose in humans) and in mice for 18 months at doses of 20, 200, or 2000 mcg/kg/day (at less than therapeutic exposure to 70 times human exposure using body surface area comparisons, based on a 65 mcg/day dose in humans). As seen with other GnRH agonists, histrelin injection administration was associated with an increase in tumors of hormonally responsive tissues. There was a significant increase in pituitary adenomas in rats at mid and high doses (2-11 times human exposure based on body surface area comparisons with a 65 mcg/day human dose). There was an increase in pancreatic islet-cell adenomas in treated female rats and a non-dose-related increase in testicular Leydig-cell tumors (highest incidence in the low-dose group). In mice, there was significant increase in mammary-gland adenocarcinomas in all treated females. In addition, there were increases in stomach papillomas in male rats given high doses, and an increase in histiocytic sarcomas in female mice at the highest dose.

Mutagenicity studies have not been performed with histrelin acetate. Saline extracts of implants with and without histrelin acetate were negative in a battery of genotoxicity studies. Fertility studies have been conducted in rats and monkeys given subcutaneous daily doses of histrelin acetate up to 180 mcg/kg/day (up to 13 and 30 times human exposure, respectively using body surface area comparisons, based on a 65 mcg/day human dose) for 6 months and full reversibility of fertility suppression was demonstrated. The development and reproductive performance of offspring from parents treated with histrelin acetate has not been investigated.

14 CLINICAL STUDIES

The efficacy of SUPPRELIN LA in children with CPP has been evaluated in two single-arm, open label studies. Study 1 was conducted in 11 pretreated female patients, 3.7 to 11.0 years of age. Study 2 was conducted in 36 patients (33 females and 3 males), 4.5 to 11.6 years of age. Sixteen pretreated and 20 treatment-naïve patients were enrolled in Study 2. Baseline patient characteristics were typical of patients with CPP. Efficacy assessments were similar in both studies and included endpoints that measured the suppression of gonadotropins (luteinizing hormone and follicle stimulating hormone) and gonadal sex steroids (estrogen in girls and testosterone in boys, respectively) on treatment. Other assessments were clinical (evidence of stabilization or regression of signs of puberty) or gonadal steroid-dependent (bone age, linear growth). In Study 2, the primary measure of efficacy was LH suppression.

In Study 2, suppression of LH was induced in all treatment naïve subjects and maintained in all pretreated subjects at Month 1 after implantation and continued through Month 12 (suppression was defined as a peak LH < 4 mIU/mL following stimulation with the GnRH analog leuprolide acetate).

Secondary efficacy hormone assessments (FSH, estradiol and testosterone) and additional efficacy assessments (bone age advancement, linear growth, clinical progression of puberty) indicated stabilization of disease. Estradiol suppression was present in all 33 girls (100%) through Month 9 and 97% at Month 12. Testosterone suppression was maintained in the three pre-treated males participating in Study 2. The SUPPRELIN LA effect on efficacy endpoints in the Study 1 was consistent with that observed in Study 2.

16 HOW SUPPLIED/STORAGE AND HANDLING

SUPPRELIN LA (NDC 67979-002-01) is supplied in a corrugated shipping carton that contains 2 inner cartons: a small one for the vial containing the SUPPRELIN LA implant, which is shipped with a cold pack inside a polystyrene cooler that must be refrigerated upon arrival, and a larger one comprising the Implantation Kit, which must not be refrigerated, for use during insertion or removal of SUPPRELIN LA.

The SUPPRELIN LA implant contains 50 mg of histrelin acetate. The SUPPRELIN LA implant carton contains a cold pack for refrigerated shipment and a small carton containing an amber plastic pouch. Inside the pouch is a glass vial with a Teflon-coated stopper and an aluminum seal, containing the implant in 2 mL of sterile 1.8% sodium chloride solution. (Note: The 3.5 mL vial is not completely filled with saline).

Upon receipt, refrigerate the small carton containing the amber plastic pouch and glass vial (with the implant inside) until the day of insertion. The implant vial should not be opened until just before the time of insertion.

SUPPRELIN LA is stable when stored refrigerated, in its sealed vial, pouch, and carton, at 2-8°C (36-46°F) until the expiration date provided. Excursion permitted to 25°C (77°F) for 7 days. Do not freeze. Protect from light.

17 PATIENT COUNSELING INFORMATION

Advise the patient to read the FDA-Approved patient labeling (Medication Guide).

Initial Agonistic Action
Patients should be advised that a transient worsening of symptoms of puberty or onset of new symptoms may occur initially. However, within 4 weeks of histrelin therapy, complete suppression of gonadal steroids occurs and manifestations of puberty decrease [see Warnings and Precautions (5.1)].

Post-insertion Care
Patients should be instructed to refrain from getting the inserted arm wet for 24 hours and from strenuous exertion of the inserted arm for 7 days after implant insertion to allow the incision to fully close. The adhesive elastic bandage can be removed at that time. The patient should not remove the surgical strips; rather, the strips should be allowed to fall off on their own after several days.

Psychiatric Adverse Events
Inform caregivers that symptoms of emotional lability, such as crying, irritability, impatience, anger, and aggression, have been observed in patients receiving GnRH agonists, including SUPPRELIN LA. Alert caregivers to the possibility of development or worsening of psychiatric symptoms, including depression, during treatment with SUPPRELIN LA [see Warnings and Precautions (5.3), Adverse Reactions (6.3)].

Convulsions
Inform caregivers that reports of convulsions have been observed in patients receiving GnRH agonists, including SUPPRELIN LA. Patients with a history of seizures, epilepsy, cerebrovascular disorders, central nervous system anomalies or tumors, and patients on concomitant medications that have been associated with convulsions may be at risk [see Warnings and Precautions (5.4)].

Severe Cutaneous Adverse Reactions
Inform patients and/or caregivers that severe cutaneous adverse reactions may occur during treatment with SUPPRELIN LA. Advise patients and/or caregivers to stop SUPPRELIN LA and immediately contact their healthcare provider if they experience signs or symptoms of severe cutaneous adverse reactions [see Warnings and Precautions (5.5)].

Pseudotumor Cerebri (Idiopathic Intracranial Hypertension)
Inform patients and caregivers that reports of pseudotumor cerebri (idiopathic intracranial hypertension) have been observed in pediatric patients receiving GnRH agonists. Advise patients and caregivers to monitor for headache, and vision issues such as blurred vision, double vision, loss of vision, pain behind the eye or pain with eye movement, ringing in the ears, dizziness, and nausea. Advise patients and caregivers to contact their healthcare provider if the patient develops any of these symptoms. [see Warnings and Precautions (5.6)].

Common Adverse Reactions
Patients should be advised to report to their physician any severe pain, redness, or swelling in and around the implant site. Infrequently, SUPPRELIN LA may be expelled from the body through the original incision site, rarely without the patient noticing. The patient should be instructed to monitor the incision site until it is healed. The patient should also return for routine checks of their condition and to ensure that SUPPRELIN LA is present and functioning in his/her body [see Adverse Reactions (6.1)].

For more information, call 1-800-462-3636 or visit www.supprelinla.com.

Manufactured for:
Endo USA
Malvern, PA 19355

© 2025 Endo, Inc. or one of its affiliates.
Revised: 09/2025

Medication Guide
SUPPRELIN® LA [Suh-Preh-Lin El-Ay]
(histrelin acetate) subcutaneous implant

What is the most important information I should know about SUPPRELIN LA?

- In the first week of treatment, SUPPRELIN LA can cause an increase in some hormones. During this time you may notice more signs of puberty in your child, including light vaginal bleeding and breast enlargement in girls. Within 4 weeks of treatment, you should see signs in your child that puberty is stopping.
- Some people who had SUPPRELIN LA placed in their arm have had the implant come through the skin (extrusion). Call your child’s doctor right away if the SUPPRELIN LA implant comes through the skin.
- Some people taking GnRH agonists like SUPPRELIN LA have had new or worsening mental (psychiatric) problems. Mental (psychiatric) problems may include emotional symptoms such as:
  - crying
  - irritability
  - restlessness (impatience)
  - anger
  - acting aggressive
  Call your child’s doctor right away if your child has any new or worsening mental symptoms or problems while taking SUPPRELIN LA.

- Some people taking GnRH agonists like SUPPRELIN LA have had seizures. The risk of seizures may be higher in people who:
  - have a history of seizures
  - have a history of epilepsy
  - have a history of brain or brain vessel (cerebrovascular) problems or tumors
  - are taking a medicine that has been connected to seizures such as bupropion or selective serotonin reuptake inhibitors (SSRIs)
  Seizures have also happened in people who have not had any of these problems.
  Call your child’s doctor right away if your child has a seizure while taking SUPPRELIN LA.

- Severe cutaneous (skin) adverse reactions can happen during treatment with GnRH agonists like SUPPRELIN LA.
  Stop SUPPRELIN LA and call your child's doctor right away if your child has any of the following signs or symptoms during treatment with SUPPRELIN LA:
  - skin rash or acne
  - blisters or sores in your mouth
  - dry skin
  - peeling of your skin
  - itching
  - fever
  - blisters on your skin
  - muscle or joint aches
  - redness or swelling of your face, hands, or soles of your feet
  - swollen glands

- Increased pressure in the fluid around the brain can happen in children taking GnRH agonist medicines including SUPPRELIN LA.
  Call your child’s doctor right away if your child has any of the following symptoms during treatment with SUPPRELIN LA:
  - headache
  - ringing in the ears
  - eye problems, including blurred vision, double vision, and decreased eyesight
  - dizziness
  - nausea
  - eye pain

What is SUPPRELIN LA?

- SUPPRELIN LA is an implanted gonadotropin releasing hormone (GnRH) medicine used for the treatment of children with central precocious puberty (CPP).
- It is not known if SUPPRELIN LA is safe and effective in children under 2 years of age.

SUPPRELIN LA should not be taken if your child is:

- allergic to gonadotropin releasing hormone (GnRH), GnRH agonist medicines, or any ingredients in the SUPPRELIN LA implant. See the end of this Medication Guide for a complete list of ingredients in SUPPRELIN LA.
- pregnant or becomes pregnant. SUPPRELIN LA can cause birth defects or loss of the baby. If your child becomes pregnant call your doctor.

Before your child receives SUPPRELIN LA, tell the doctor about all of your child’s medical conditions, including if they:

- have a history of mental (psychiatric) problems.
- have a history of seizures.
- have a history of epilepsy.
- have a history of brain or brain vessel (cerebrovascular) problems or tumors.
- are taking a medicine that has been connected to seizures such as bupropion or selective serotonin reuptake inhibitors (SSRIs).

Tell your doctor about all the medicines your child takes, including prescription and over-the-counter medicines, vitamins, and herbal supplements.

How will your child receive SUPPRELIN LA?

- Your child’s doctor should do tests to make sure your child has CPP before treating with SUPPRELIN LA.
- SUPPRELIN LA lasts for 12 months. One implant will give the medicine for 12 months. After 12 months, the SUPPRELIN LA implant must be removed. The doctor may place a new SUPPRELIN LA implant at this time to continue treatment.
- SUPPRELIN LA is placed under the skin of the inside of the upper arm. The doctor will numb the arm of your child, make a small cut, and then place the SUPPRELIN LA implant under the skin. The cut may be closed with stitches or surgical strips and covered with a pressure bandage.
- Your child should keep the arm clean and dry and should not swim or bathe for 24 hours after receiving the SUPPRELIN LA implant. The bandage can be removed after 24 hours. Do not remove any surgical strips. Surgical strips will fall off on their own in a few days.
- Your child should avoid heavy play or exercise that uses the arm where the implant was placed for 7 days. After the cut has healed, your child can go back to his or her normal activities. The doctor will give you complete instructions.
- Keep all scheduled visits to the doctor. The doctor will do regular exams and blood tests to check for signs of puberty.
- Sometimes the doctor will have to do special tests, such as an ultrasound, computed tomography (CT) scan, or magnetic resonance imaging (MRI) if the SUPPRELIN LA implant is hard to find under your child’s skin.

What are the possible side effects of SUPPRELIN LA?

SUPPRELIN LA may cause serious side effects. See “What is the most important information I should know about SUPPRELIN LA?”

The most common side effect of SUPPRELIN LA includes skin reactions at the place where the implant is inserted. These reactions may include pain, redness, bruising, soreness, and swelling in and around the implant site. Call your child’s doctor if your child has bleeding, redness, or severe pain where the implant was inserted.

These are not all the possible side effects of SUPPRELIN LA. Call your doctor for medical advice about side effects. You may report side effects to FDA at 1-800-FDA-1088.

What are the ingredients in SUPPRELIN LA?

Active ingredient: histrelin acetate

Inactive ingredients: stearic acid NF, hydrogel polymer reservoir composed of 2-hydroxyethyl methacrylate, 2-hydroxypropyl methacrylate, trimethylolpropane trimethacrylate, benzoin methyl ether, Perkadox-16, and Triton X-100

Manufactured for: Endo USA, Malvern, PA 19355, www.endo.com or call 1-800-462-3636.

This Medication Guide has been approved by the U.S. Food and Drug Administration.

© 2025 Endo, Inc. or one of its affiliates.

Rev:09/2025

Package Label – Principle Display Panel – Vial Label

Package Label – Principle Display Panel – Carton Label